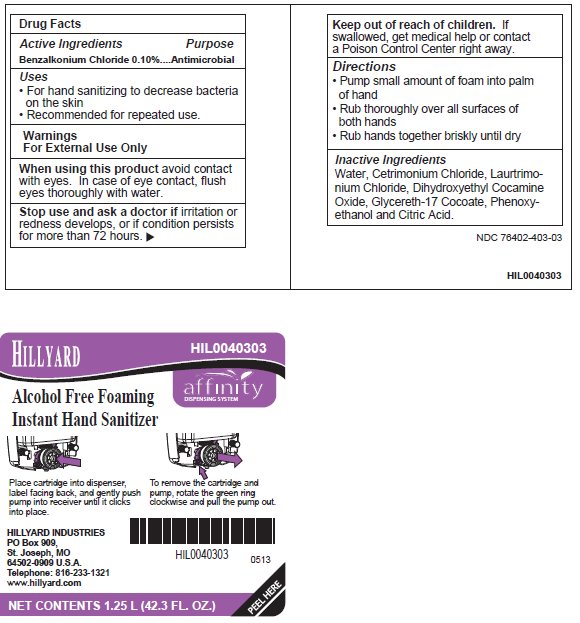 DRUG LABEL: Hillyard Alcohol Free Foaming Instant Hand Sanitizer
NDC: 76402-403 | Form: LIQUID
Manufacturer: Hillyard GMP
Category: otc | Type: HUMAN OTC DRUG LABEL
Date: 20241230

ACTIVE INGREDIENTS: BENZALKONIUM CHLORIDE 0.1 g/100 mL
INACTIVE INGREDIENTS: WATER; CETRIMONIUM CHLORIDE; LAURTRIMONIUM CHLORIDE; DIHYDROXYETHYL COCAMINE OXIDE; GLYCERETH-17 COCOATE; PHENOXYETHANOL; ANHYDROUS CITRIC ACID

Hillyard Alcohol Free Foaming Instant Hand Sanitizer

Active ingredient

Benzalkonium Chloride 0.10%

Purpose

Antimicrobial

Uses

- For hand sanitizing to decrease bacteria on the skin
- Recommended for repeated use.

Warnings

- For External Use Only

When using this product

avoid contact with eyes. In case of eye contact, flush eyes thoroughly with water.

Stop use and ask a doctor if

irritation or redness develops, or if condition persists for more than 72 hours.

Keep Out of Reach of Children

If swallowed, get medical help or contact a Poison Control Center right away.

Directions

- Pump small amount of foam into palm of hand
- Rub thoroughly over all surfaces of both hands
- Rub hands together briskly until dry

Inactive Ingredients

Water, Cetrimonium Chloride, Laurtrimonium Chloride, Dihydroxyethyl Cocamine Oxide, Glycereth-17 Cocoate, Phenoxyethanol and Citric Acid.

Package/Label Principal Display Panel

Hillyard
Alcohol Free Foaming
Instant Hand Sanitizer

HIL0040303

affinity
DISPENSING SYSTEM

Place cartridge into dispenser, label facing back, and gently push pump into receiver until it clicks into place.

To remove the cartridge and pump, rotate the green ring clockwise and pull the pump out.

HILLYARD INDUSTRIES
PO Box 909,
St. Joseph, MO
64502-0909 U.S.A.
Telephone: 816-233-1321
www.hillyard.com

NET CONTENTS 1.25 L (42.3 FL. OZ.)
PEEL HERE

Carton Label